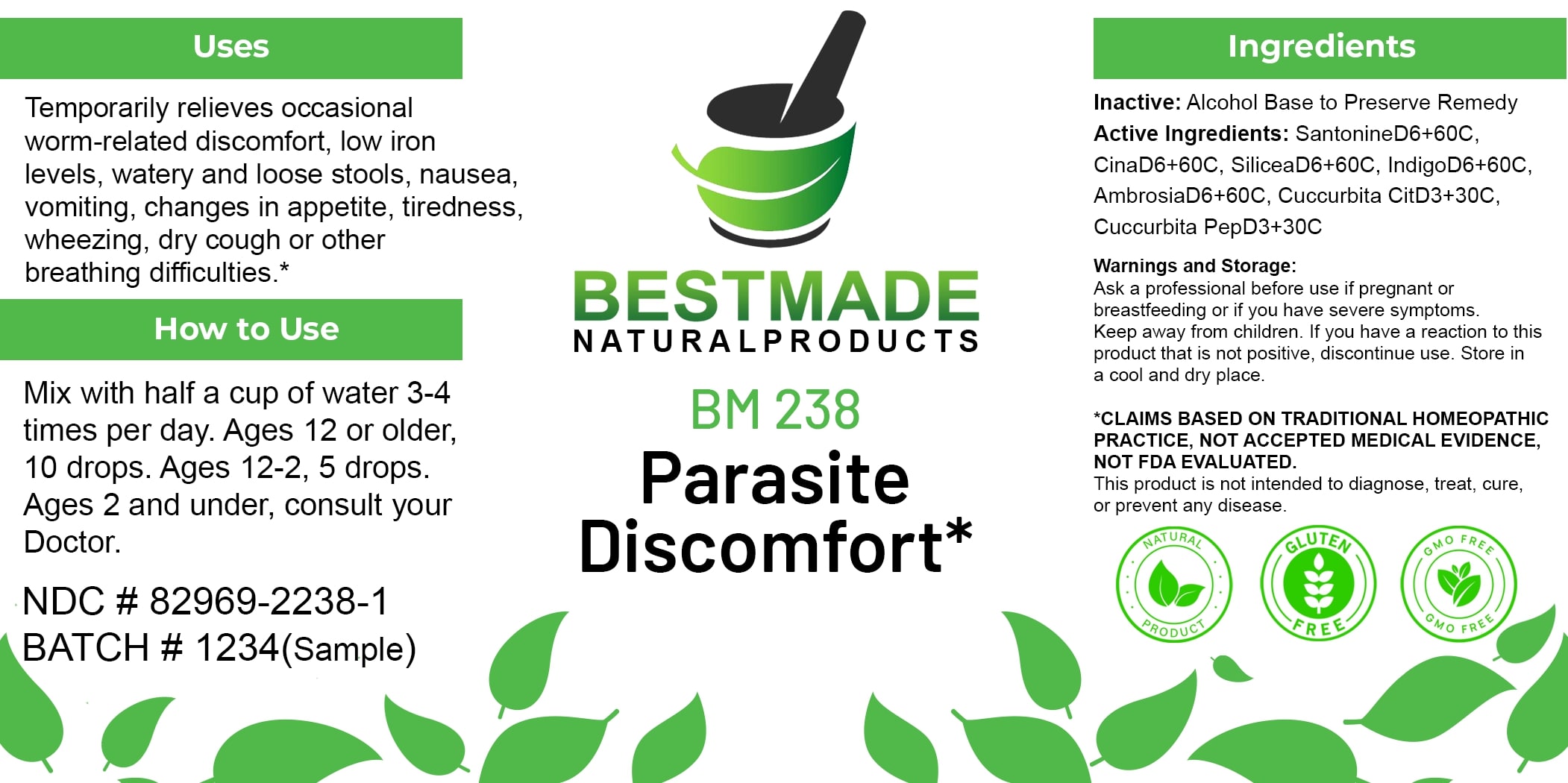 DRUG LABEL: Bestmade Natural Products BM238
NDC: 82969-2238 | Form: LIQUID
Manufacturer: Bestmade Natural Products
Category: homeopathic | Type: HUMAN OTC DRUG LABEL
Date: 20250326

ACTIVE INGREDIENTS: ARTEMISIA CINA FLOWER 30 [hp_C]/30 [hp_C]; SILICA 30 [hp_C]/30 [hp_C]; CUCURBITA PEPO WHOLE 30 [hp_C]/30 [hp_C]; INDIGO 30 [hp_C]/30 [hp_C]; WATERMELON SEED 30 [hp_C]/30 [hp_C]; SANTONIN 30 [hp_C]/30 [hp_C]; AMBROSIA ARTEMISIIFOLIA WHOLE 30 [hp_C]/30 [hp_C]
INACTIVE INGREDIENTS: ALCOHOL 30 [hp_C]/30 [hp_C]

BM238

DOSAGE AND ADMINISTRATION

How to Use

Mix with half a cup of water 3-4 times per day. Ages 12 or older, 10 drops. Ages 12-2, 5 drops. Ages 2 and under, consult your Doctor.

Uses

Temporarily relieves occasional worm-related discomfort, low iron levels, watery and loose stools, nausea, vomiting, changes in appetite, tiredness, wheezing, dry cough or other breathing difficulties.*

*CLAIMS BASED ON TRADITIONAL HOMEOPATHIC PRACTICE, NOT ACCEPTED MEDICAL EVIDENCE, NOT FDA EVALUATED.

This product is not intended to diagnose, treat, cure, or prevent any disease.

INACTIVE INGREDIENT

Ingredients

Inactive: Alcohol Base to Preserve Remedy

ACTIVE INGREDIENT

Active Ingredients: SantonineD6+60C, CinaD6+60C, SiliceaD6+60C, IndigoD6+60C, AmbrosiaD6+60C, Cuccurbita CitD3+30C, Cuccurbita PepD3+30C

KEEP OUT OF REACH OF CHILDREN

Warnings and Storage:

Ask a professional before use if pregnant or breastfeeding or if you have severe symptoms. Keep away from children. If you have a reaction to this product that is not positive, discontinue use. Store in a cool and dry place.

Uses

Temporarily relieves occasional worm-related discomfort, low iron levels, watery and loose stools, nausea, vomiting, changes in appetite, tiredness, wheezing, dry cough or other breathing difficulties.*

*CLAIMS BASED ON TRADITIONAL HOMEOPATHIC PRACTICE, NOT ACCEPTED MEDICAL EVIDENCE, NOT FDA EVALUATED.

This product is not intended to diagnose, treat, cure, or prevent any disease.

Warnings and Storage:

Ask a professional before use if pregnant or breastfeeding or if you have severe symptoms. Keep away from children. If you have a reaction to this product that is not positive, discontinue use. Store in a cool and dry place.

*CLAIMS BASED ON TRADITIONAL HOMEOPATHIC PRACTICE, NOT ACCEPTED MEDICAL EVIDENCE, NOT FDA EVALUATED.

This product is not intended to diagnose, treat, cure, or prevent any disease.

Entire package label